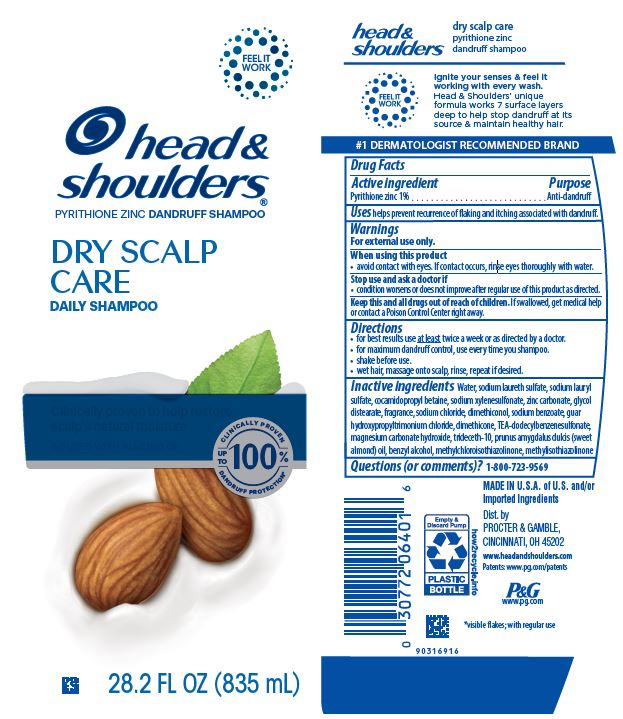 DRUG LABEL: Head and Shoulders
NDC: 37000-092 | Form: LOTION/SHAMPOO
Manufacturer: The Procter & Gamble Manufacturing Company
Category: otc | Type: HUMAN OTC DRUG LABEL
Date: 20251231

ACTIVE INGREDIENTS: PYRITHIONE ZINC 1 g/100 mL
INACTIVE INGREDIENTS: DIMETHICONOL GUM; TRIDECETH-10; TRIETHANOLAMINE DODECYLBENZENESULFONATE; GUAR HYDROXYPROPYLTRIMONIUM CHLORIDE (1.7 SUBSTITUENTS PER SACCHARIDE); WATER; SODIUM LAURETH-3 SULFATE; SODIUM LAURYL SULFATE; DIMETHICONE; ZINC CARBONATE; GLYCOL DISTEARATE; SODIUM XYLENESULFONATE; SODIUM CHLORIDE; SODIUM BENZOATE; MAGNESIUM CARBONATE HYDROXIDE; ALMOND OIL; METHYLCHLOROISOTHIAZOLINONE; METHYLISOTHIAZOLINONE; BENZYL ALCOHOL; COCAMIDOPROPYL BETAINE

Head and Shoulders®
Dry Scalp Care

Drug Facts

Active ingredient

Pyrithione zinc 1%

Purpose

Anti-dandruff

Uses

helps prevent recurrence of flaking and itching associated with dandruff.

Warnings

For external use only.

When using this product

- avoid contact with eyes. If contact occurs, rinse eyes thoroughly with water.

Stop use and ask a doctor if

- condition worsens or does not improve after regular use of this product as directed.

KEEP OUT OF REACH OF CHILDREN

Keep this and all drugs out of reach of children. If swallowed, get medical help or contact a Poison Control Center right away.

Directions

- for best results use at least twice a week or as directed by a doctor.
- for maximum dandruff control, use every time you shampoo.
- shake before use.
- wet hair, massage onto scalp, rinse, repeat if desired.

Inactive ingredients

Water, sodium laureth sulfate, sodium lauryl sulfate, cocamidopropyl betaine, sodium xylenesulfonate, zinc carbonate, glycol distearate, fragrance, sodium chloride, dimethiconol, sodium benzoate, guar hydroxypropyltrimonium chloride, dimethicone,TEA-dodecylbenzenesulfonate, magnesium carbonate hydroxide, trideceth-10, prunus amygdalus dulcis (sweet almond) oil, benzyl alcohol, methylchloroisothiazolinone, methylisothiazolinone

Questions (or comments)?

1-800-723-9569

Dist. by PROCTER & GAMBLE,
CINCINNATI, OH 45202

PRINCIPAL DISPLAY PANEL - 835mL Bottle Label

head &
shoulders®
pyrithione zinc dandruff shampoo

DRY SCALP CARE
Daily Shampoo

CLINICALLY PROVEN TO HELP
RESTORE SCALP'S NATURAL MOISTURE
INFUSED WITH ALMOND OIL

FLAKE FREE.*
UP TO 100%
GUARANTEED^

28.2 FL OZ (835 mL)